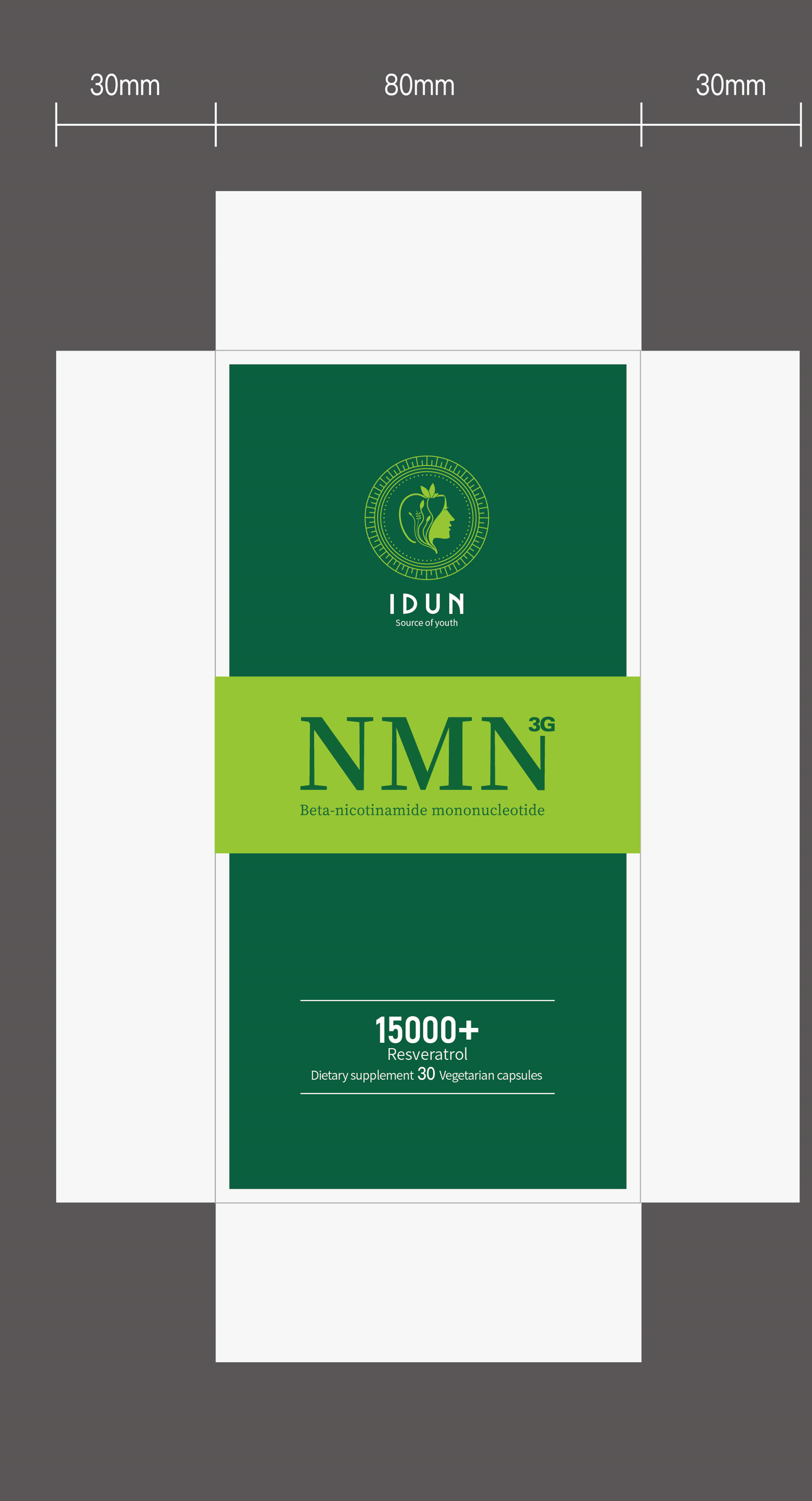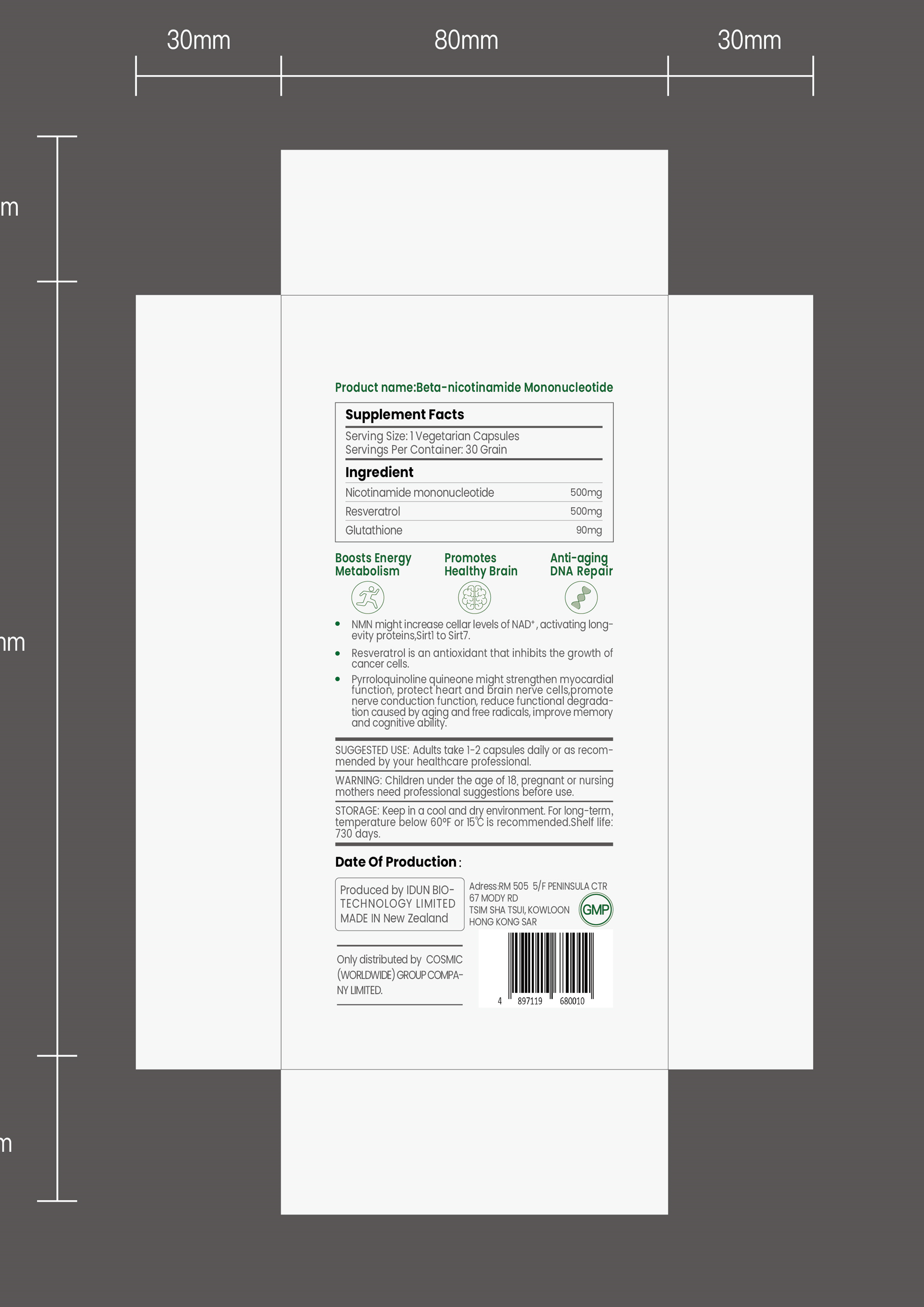 DRUG LABEL: NMN
NDC: 82042-003 | Form: CAPSULE
Manufacturer: IDun Bio-Technology Limited
Category: otc | Type: HUMAN OTC DRUG LABEL
Date: 20210908

ACTIVE INGREDIENTS: RESVERATROL 45.8 mg/100 1; NICOTINAMIDE MONONUCLEOTIDE 45.8 mg/100 1
INACTIVE INGREDIENTS: GLUTATHIONE

ACTIVE INGREDIENT

Nicotinamide mononucleotide(45.8%)

resveratrol(45.8%)

KEEP OUT OF REACH OF CHILDREN

Children under the age of 18 need professional suggestions before use.

PURPOSE

Boosts Energy Metabolism
Promotes Healthy Brain
Anti-aging DNA Repair

INACTIVE INGREDIENT

Glutathione

INDICATIONS AND USAGE

NMN might increase cellar levels of NAD+ , activating long-evity proteins,Sirtl to Sirt7.Resveratrol is an antioxidant that inhibits the growth ofcancer cells.
Pyrroloquinoline quineone might strengthen myocardial function, protect'heart and brain nerve cells,promotenerve conduction function, reduce functional degrada-tion caused by aging and free radicals, improve memoryand cognitive'ability.

SUGGESTED USE

Adults take 1-2 capsules daily or as recom-mended by your healthcare professional.

STORAGE AND HANDLING

Keep in a cool and dry environment.For long-term,temperature below 60°F or 15℃ is recommended.

WARNINGS

Children under the age of 18, pregnant or nursing mothers need professional suggestions before use.